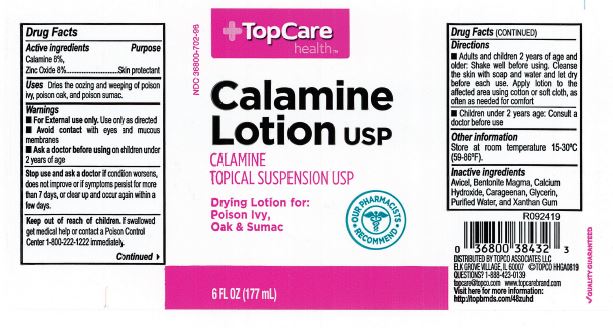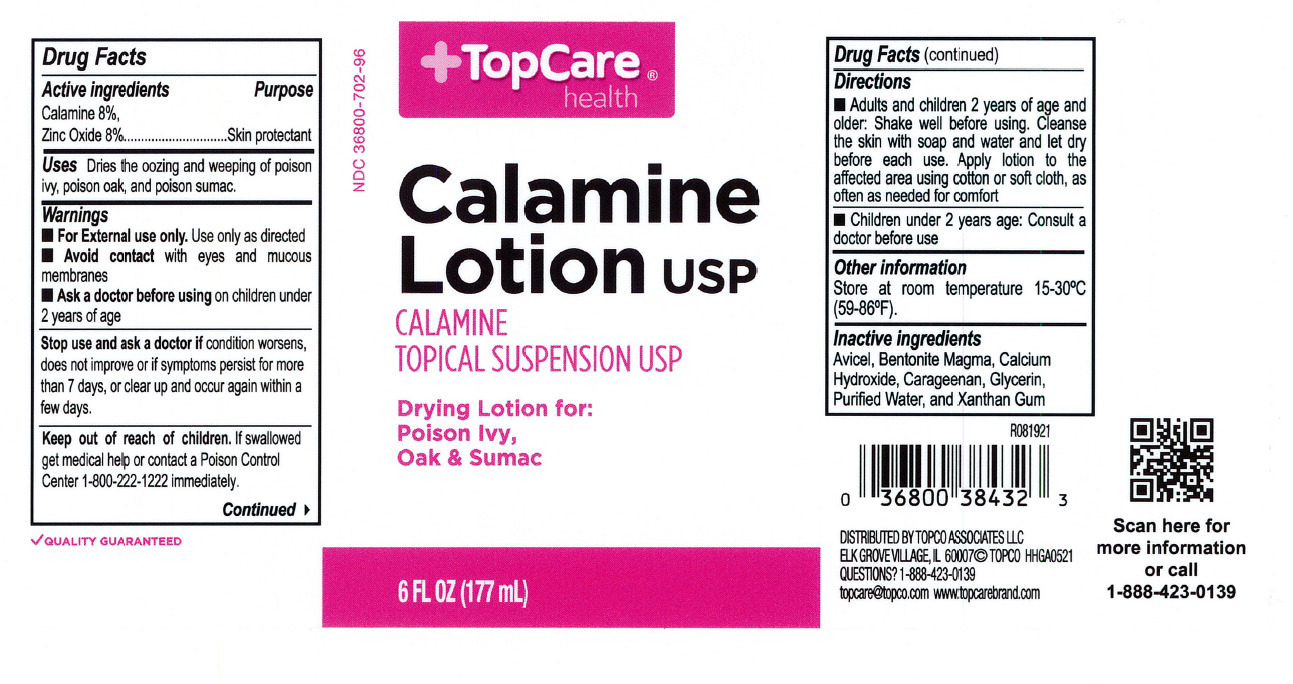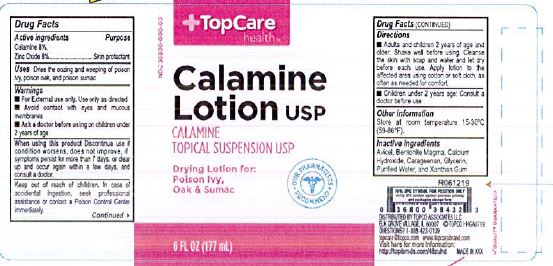 DRUG LABEL: TopCare Calamine
NDC: 36800-702 | Form: LOTION
Manufacturer: TOPCO ASSOCIATES LLC
Category: otc | Type: HUMAN OTC DRUG LABEL
Date: 20231218

ACTIVE INGREDIENTS: ZINC OXIDE 160 mg/1 mL
INACTIVE INGREDIENTS: BENTONITE; CARRAGEENAN; XANTHAN GUM; WATER; CALCIUM HYDROXIDE; MICROCRYSTALLINE CELLULOSE; GLYCERIN

Top Care Calamine Lotion

ACTIVE INGREDIENT

Calamine 8% and Zinc Oxide 8%

PURPOSE

Skin protectant

INDICATIONS AND USAGE

dries the oozing and weeping o poison ivy, poison oak, and poison sumac.

WARNINGS

For external use only. Use only as directed.

Avoid contact with eyes and mucous membranes.

Ask a doctor before using on chilren 2 years of age.

KEEP OUT OF REACH OF CHILDREN

In case of accidental ingestion, seek professional assistance or contact a Poison Control center immediately.

DOSAGE AND ADMINISTRATION

Adults and chidren 2 years of age and older: shake well before using. Cleanse the skin with soap and water and let it dry befroe each use. Apply lotion to the affected area using a cotton or soft cloth, as often as needed for comfort.

Children under 2 years of age: Consult a doctor before use.

Directions

Children under 2 years of age: Consult a doctor before use (8/2021)

INACTIVE INGREDIENT

Bentonite magma, calcium hydroxide, glycerin, purified water.